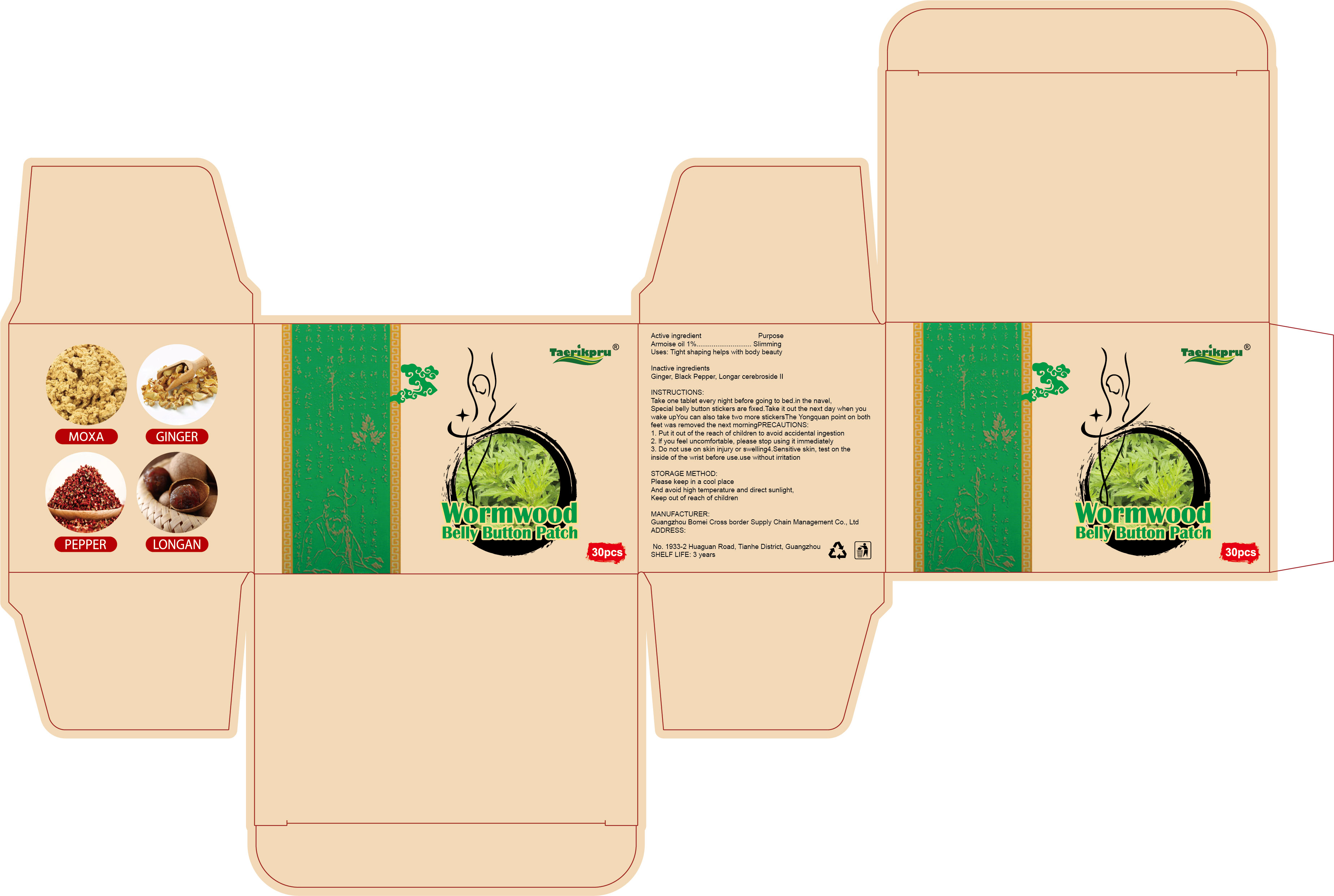 DRUG LABEL: Wormwood Belly Button Patch
NDC: 84537-004 | Form: PATCH
Manufacturer: Guangzhou Bomei Cross border Supply Chain Management Co., Ltd
Category: otc | Type: HUMAN OTC DRUG LABEL
Date: 20240923

ACTIVE INGREDIENTS: ARTEMISIA VULGARIS TOP OIL 0.01 g/1 1
INACTIVE INGREDIENTS: BLACK PEPPER; LONGAN CEREBROSIDE II; BAICALIN; GINGER

Wormwood Belly Button Patch

ACTIVE INGREDIENT

Armoise oil 1%

PURPOSE

Slimming

KEEP OUT OF REACH OF CHILDREN

Put it out of the reach of children to avoid accidental ingestion

INDICATIONS AND USAGE

Uses: Tight shaping helps with body beauty

WARNINGS

1. Put it out of the reach of children to avoid accidental ingestion

2. lf you feel uncomfortable, please stop using it immediately

3. Do not use on skin injury or swelling

4.Sensitive skin, test on theinside of the wrist before use.use without irritation

DOSAGE AND ADMINISTRATION

INSTRUCTIONS:Take one tablet every night before going to bed.in the navel,Special belly button stickers are fixed.Take it out the next day when youwake upYou can also take two more stickersThe Yongquan point on bothfeet was removed the next morning

STORAGE AND HANDLING

STORAGE METHOD:Please keep in a cool placeAnd avoid high temperature and direct sunlight,Keep out of reach of children

INACTIVE INGREDIENT

GINGER
BLACK PEPPER
BAICALIN
LONGAN CEREBROSIDE II